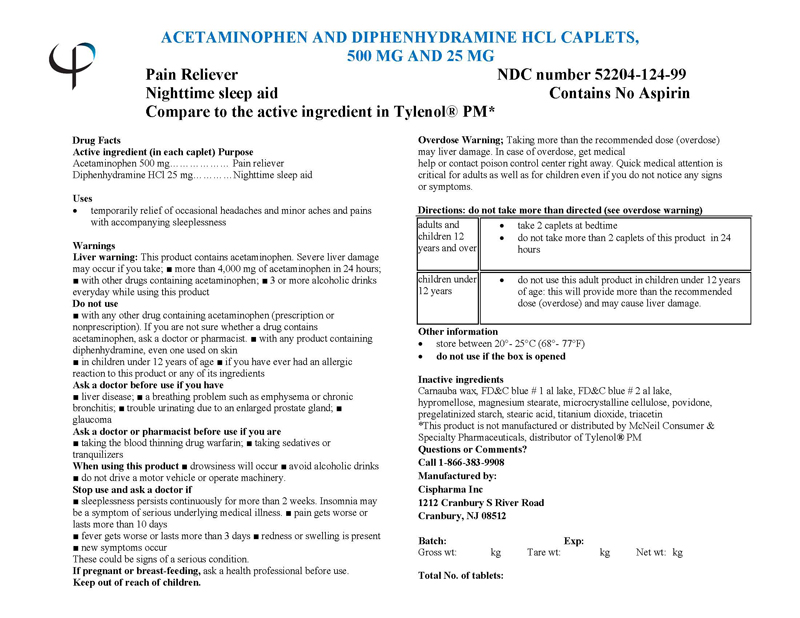 DRUG LABEL: ACETAMINOPHEN AND DIPHENHYDRAMINE HYDROCHLORIDE
NDC: 52204-124 | Form: TABLET
Manufacturer: Cispharma, Inc
Category: otc | Type: HUMAN OTC DRUG LABEL
Date: 20110328

ACTIVE INGREDIENTS: ACETAMINOPHEN 500 mg/1 1; DIPHENHYDRAMINE HYDROCHLORIDE 25 mg/1 1
INACTIVE INGREDIENTS: CARNAUBA WAX; FD&C BLUE NO. 1; FD&C BLUE NO. 2; HYPROMELLOSES; MAGNESIUM STEARATE; CELLULOSE, MICROCRYSTALLINE; POVIDONE; STARCH, CORN; STEARIC ACID; TITANIUM DIOXIDE; TRIACETIN

ACETAMINOPHEN AND DIPHENHYDRAMINE HYDROCHLORIDE CAPLETS

Drug Facts

Active ingredient (in each caplet)

Acetaminophen ..............................500 mg

Diphenhydramine HCl ......................25 mg

PURPOSE

Pain Reliver

Nighttime Sleep Aid

Uses

temporarily relief of occasional headaches and minor aches and pains with accompanying sleeplessness

Warnings

Liver warning: This product contains acetaminophen. Severe liver damage may occur if you take; ■ more than 4,000 mg of acetaminophen in 24 hours; ■ with other drugs containing acetaminophen; ■ 3 or more alcoholic drinks everyday while using this product

Do not use

■ with any other drug containing acetaminophen (prescription or nonprescription). If you are not sure whether a drug contains acetaminophen, ask a doctor or pharmacist. ■ with any product containing diphenhydramine, even one used on skin ■ in children under 12 years of age ■ if you have ever had an allergic reaction to this product or any of its ingredients

Ask a doctor before use if you have

■ liver disease; ■ a breathing problem such as emphysema or chronic bronchitis; ■ trouble urinating due to an enlarged prostate gland; ■ glaucoma

Ask a doctor or pharmacist before use if you are

■ taking the blood thinning drug warfarin; ■ taking sedatives or tranquilizers

When using this product■ drowsiness will occur ■ avoid alcoholic drinks ■ do not drive a motor vehicle or operate machinery.

Stop use and ask a doctor if

■ sleeplessness persists continuously for more than 2 weeks. Insomnia may be a symptom of serious underlying medical illness. ■ pain gets worse or lasts more than 10 days

■ fever gets worse or lasts more than 3 days ■ redness or swelling is present

■ new symptoms occur

These could be signs of a serious condition.

INDICATIONS AND USAGE

Indicated for pain relief and night time sleep aid.

PREGNANCY OR BREAST FEEDING

If pregnant or breast-feeding, ask a health professional before use.

Keep out of reach of children.

Overdasage Warnings;

Taking more than the recommended dose (overdose) may liver damage. In case of overdose, get medical help or contact poison control center right away. Quick medical attention is critical for adults as well as for children even if you do not notice any signs or symptoms.

Directions: do not take more than directed (see overdose warning)

adults and children 12 years and over | - 2 caplets at bedtime - do not take more than 2 caplets of this product in 24 hours
children under 12 years | - do not use this adult product in children under 12 years of age: this will provide more than the recommended dose (overdose) and may cause liver damage.

Other Information

- store between 20°- 25°C (68°- 77°F)
- do not use if the box is opened

Inactive Ingredients

Carnauba wax, FD&C blue # 1 al lake, FD&C blue # 2 al lake, hypromellose, magnesium stearate, microcrystalline cellulose, povidone, pregelatinized starch, stearic acid, titanium dioxide, triacetin

*This product is not manufactured or distributed by McNeil Consumer & Specialty Pharmaceuticals, distributor of Tylenol® PM

Questions or Comments?
Call 1-866-383-9908

Manufactured by:

Cispharma Inc
1212 Cranbury S River Road
Cranbury, NJ 08512